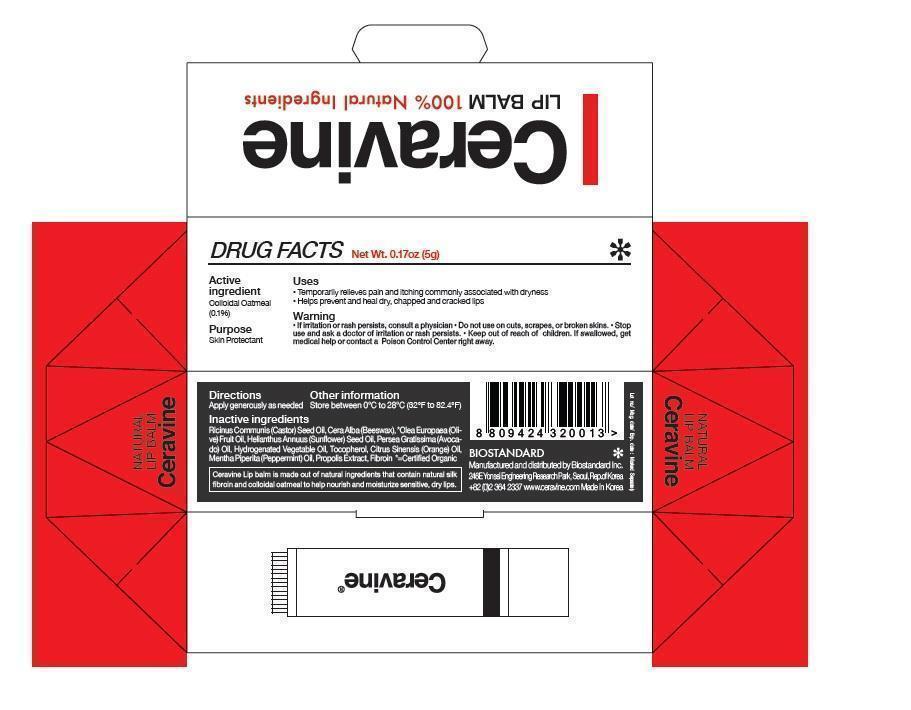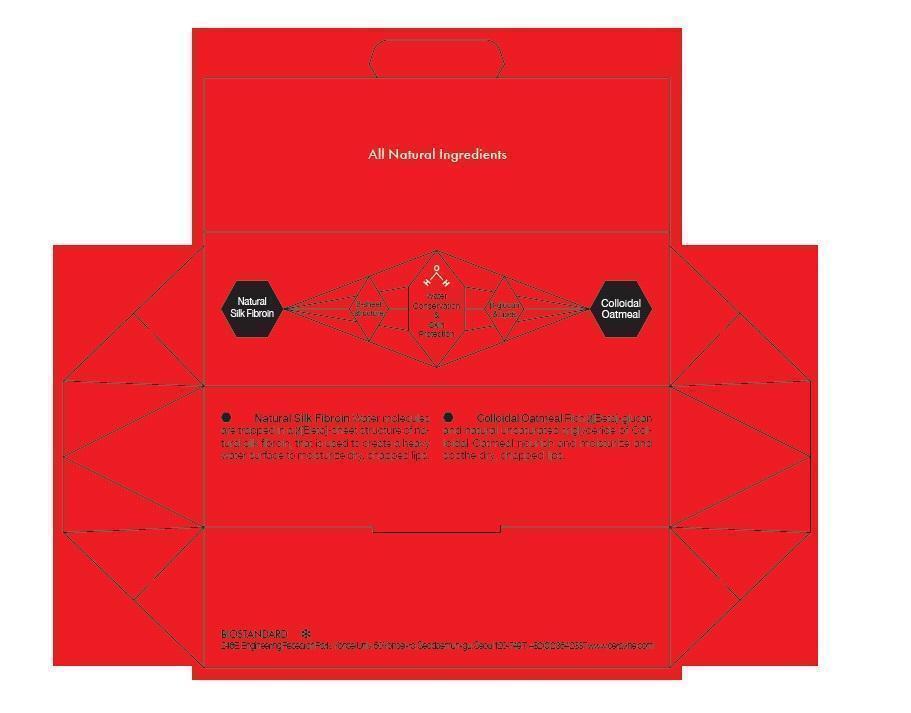 DRUG LABEL: Ceravine Lip Balm
NDC: 61403-030 | Form: STICK
Manufacturer: Biostandard Inc.
Category: otc | Type: HUMAN OTC DRUG LABEL
Date: 20150804

ACTIVE INGREDIENTS: OATMEAL 0.0003 g/5 g
INACTIVE INGREDIENTS: CASTOR OIL; YELLOW WAX; OLIVE OIL; SUNFLOWER OIL; AVOCADO OIL; TOCOPHEROL; ORANGE OIL; PEPPERMINT OIL; PROPOLIS WAX

Drug Facts

Active ingredient

Colloidal Oatmeal (0.1%)

Purpose

Skin Protectant

Uses

- Temporarily relieves pain and itching commonly associated with dryness
- Helps prevent and heal dry; chapped and cracked lips

Warnings

- If irritation or rash persists, consult a physician

Do not use on

cuts, scrapes, or broken skins

Stop use and ask a doctor

if irritation or rash persists.

Keep out of reach of children.

If swallowed, get medical help or contact a Poison Control Center right away.

Directions

Apply generously as needed.

Other information

Store between 0 C to 28 C (62 F to 82.4 F)

Inactive ingredients

Ricinus Communis (Castor) Seed Oil, Cera Alba (Beeswax), Olea Europaea (Olive) Fruit Oil, Helianthus Annus (Sunflower) Seed Oil, Persea Gratissima (Avocado) Oil, Hydrogenated Vegetable Oil, Tocopherol, Citrus Sinensis (Orange) Oil, Mentha Piperita (Peppermint) Oil, Propolis Extract, Fibroin

Principal Display Panel

Ceravine LIP BALM

100% Natural Ingredients

Net Wt. 0.17 oz (5g)